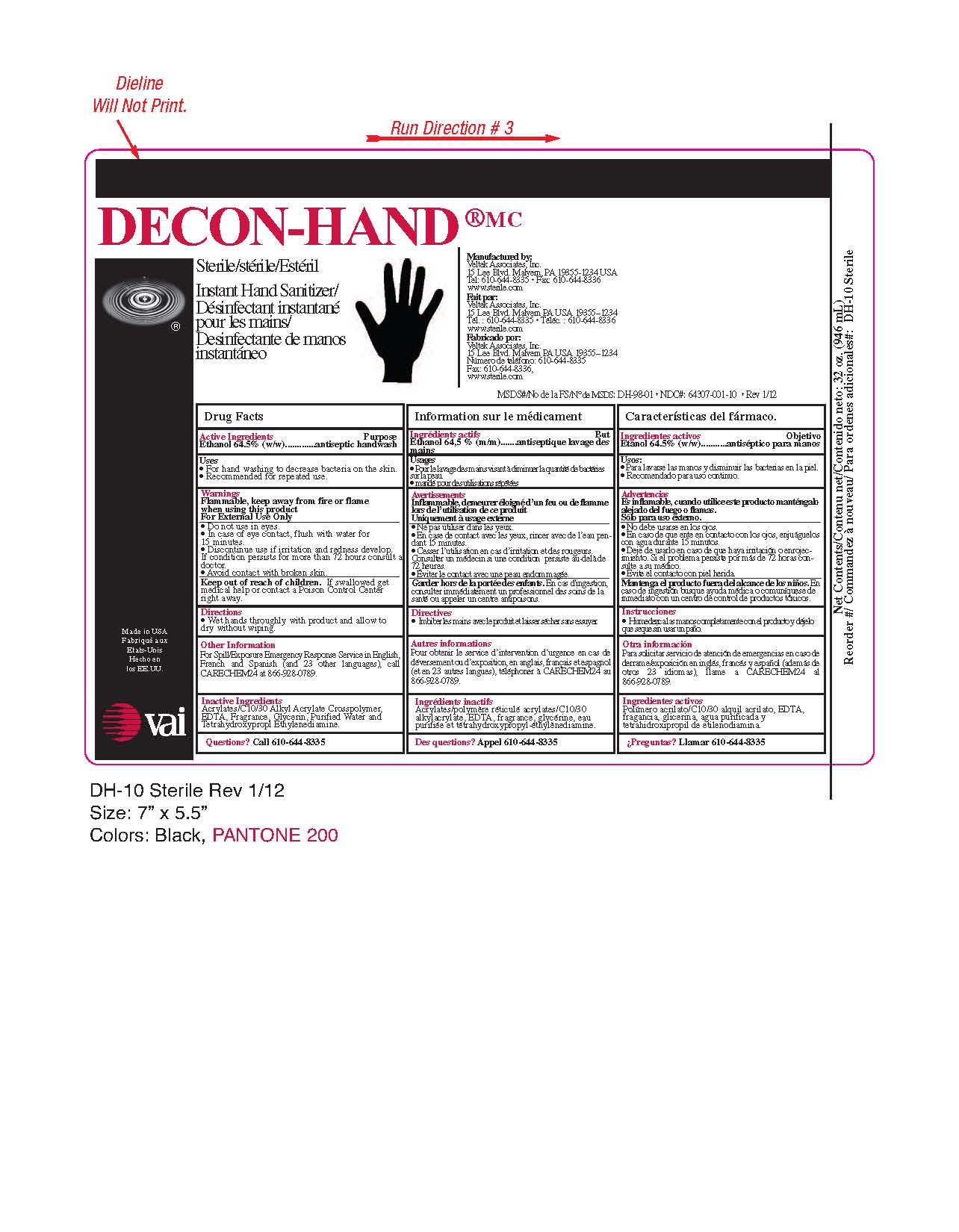 DRUG LABEL: Decon Hand Instant Hand Sanitizer
NDC: 64307-001 | Form: LIQUID
Manufacturer: Veltek Associates, Inc.
Category: otc | Type: HUMAN OTC DRUG LABEL
Date: 20231015

ACTIVE INGREDIENTS: ALCOHOL 64.5 mL/100 mL
INACTIVE INGREDIENTS: CARBOMER INTERPOLYMER TYPE A (55000 CPS); EDETIC ACID; GLYCERIN; WATER; EDETOL

Drug Facts

Purpose

Antiseptic Handwash

Active Ingredients

Ethanol 64.5 (w/w)

Uses

- For hand washing to decrease bacteria on the skin.
- Recommended for repeated use.

Warnings

Flammable, keep away from fire or flame when using this product

For External Use Only

- Do not use in eyes.
- In case of eye contact, flush with water for 15 minutes.
- Discontinue use if irritation and redness develop. If condition persists for more than 72 hours consult a doctor.
- Avoid contact with broken skin.

Keep out of reach of children. If swallowed get medical help or contact a Poison Control Center right away.

Directions

- Wet hands thoroughly with product and allow to dry without wiping.

Other Information

For Spill/Exposure Emergency Response Service in English, French and Spanish (and 23 other languages), call CARECHEM24 at 866-928-0789.

Inactive Ingredients

Acrylates/C10/30 Alkyl Acrylate Crosspolymer, EDTA, Fragrance, Glycerin, Purified Water and Tetrahydroxypropyl Ethylenediamine.

Questions?

Call 610-644-8335

PACKAGE LABEL

Place holder text